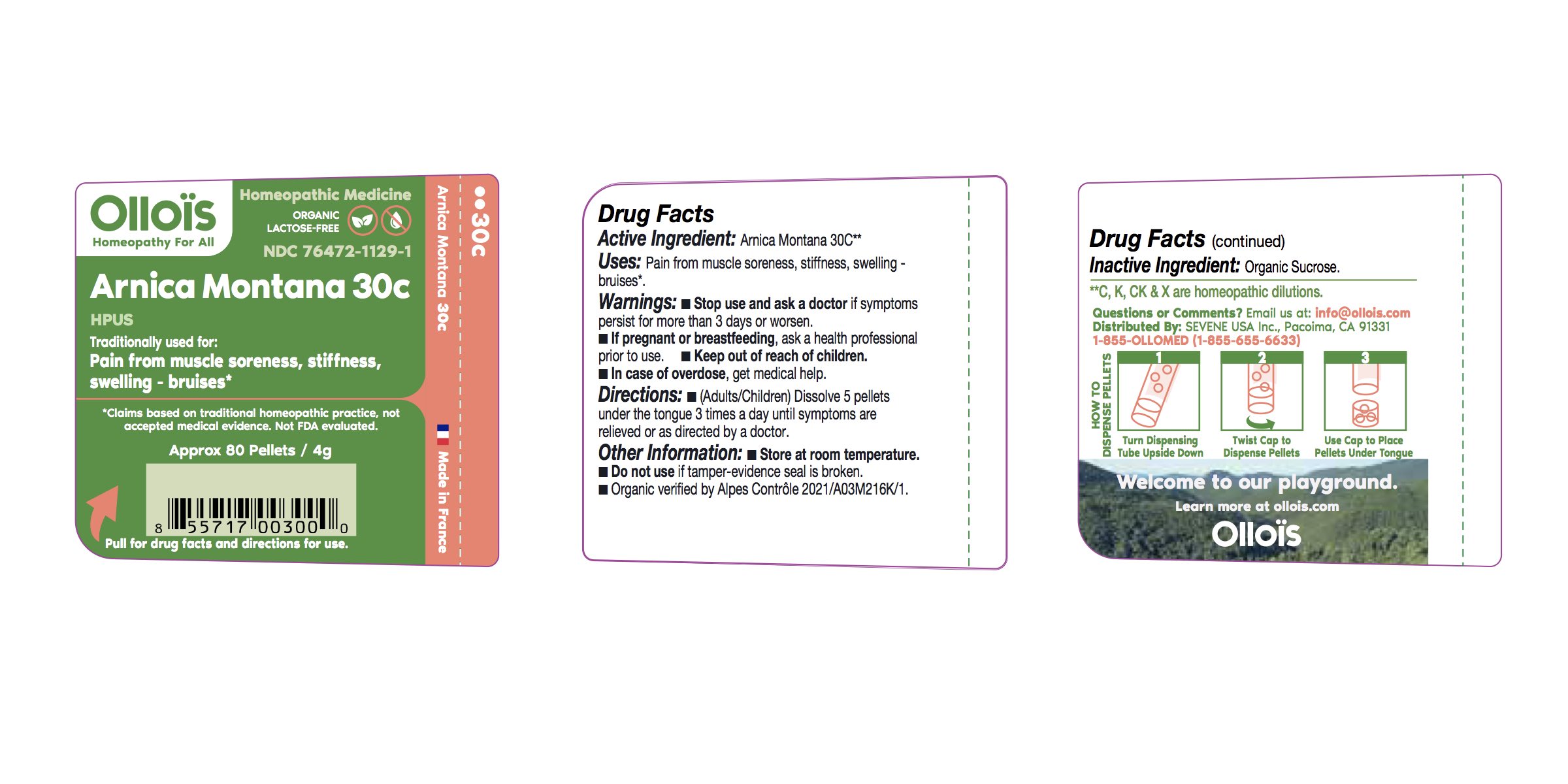 DRUG LABEL: ARNICA 30C
NDC: 76472-1129 | Form: PELLET
Manufacturer: SEVENE USA
Category: homeopathic | Type: HUMAN OTC DRUG LABEL
Date: 20250210

ACTIVE INGREDIENTS: ARNICA MONTANA 30 [hp_C]/1 1
INACTIVE INGREDIENTS: SUCROSE

Sevene USA (as PLD) - ARNICA MONTANA 30C (76472-1129)

ACTIVE INGREDIENT

HOMEOPATHIC DILUTION OF HPUS ARNICA MONTANA 30C

PURPOSE

TRADITIONALLY USED FOR: PAIN FROM TRAUMA - BRUISES - STIFFNESS - MUSCLE SORENESS.

DIRECTIONS

(adults/children) Dissolve 5 pellets under the tongue 3 times a day until symptoms are relieved or as directed by a physician.

USE:

Condition listed above or as directed by a physician.

WARNINGS

Stop use and ask a physician if symptoms persist for more than 3 days or worsen.

PREGNANCY OR BREAST FEEDING

If pregnant or breast-feeding, ask a health professional before use.

Keep out of reach of children.

OTHER INFORMATION

Store at room temperature.

Do not use if pellet-dispenser seal is broken.

INACTIVE INGREDIENTS:

Sucrose.

QUESTIONS?

info@ollois.com

- WWW.OLOIS.COM
- Made in France.

Not reviewed by the FDA and not guaranteed to be effective. This homeopathic dilution may not be susceptible to scientific measurement.